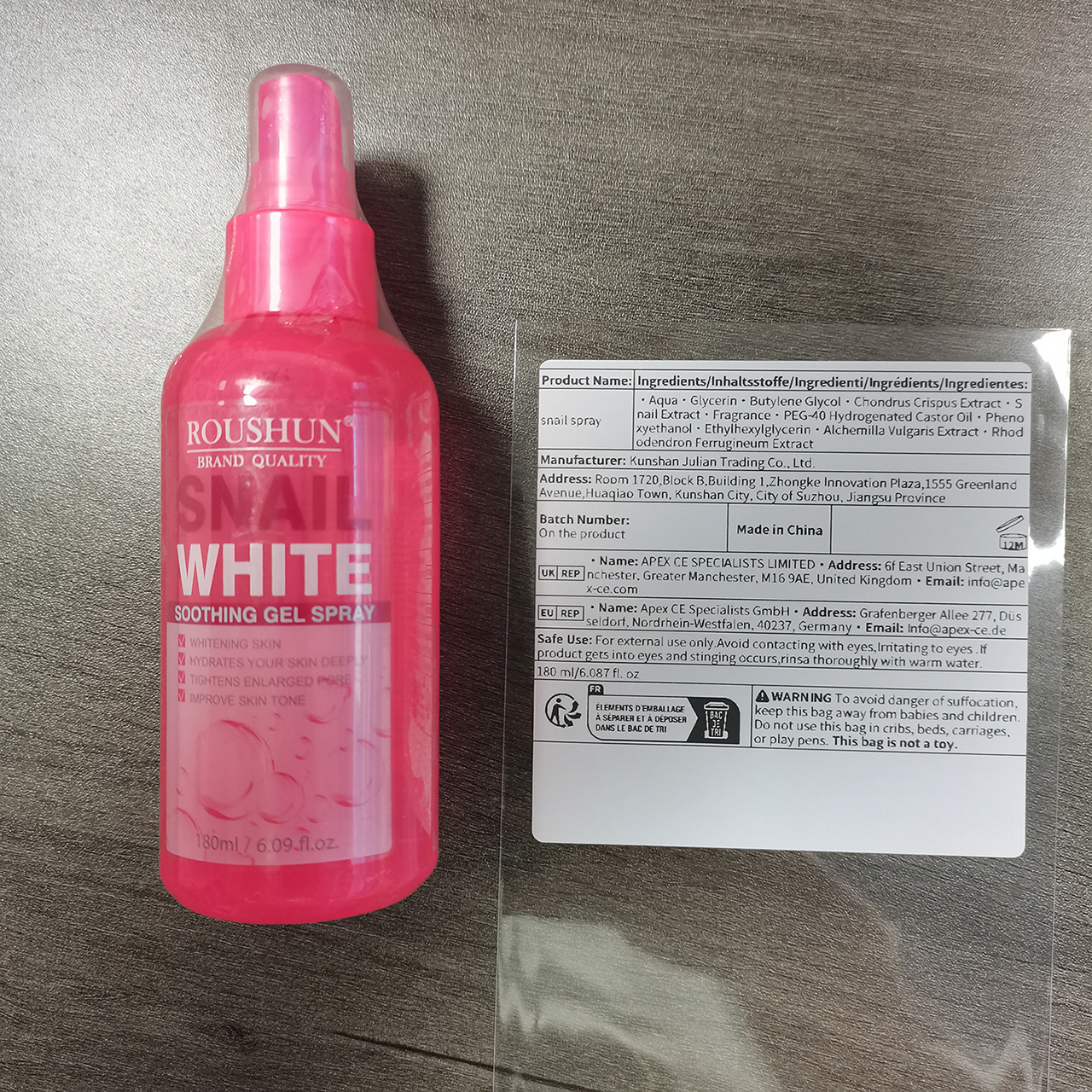 DRUG LABEL: snail
NDC: 84551-014 | Form: SPRAY
Manufacturer: Kunshan Julian Trading Co., Ltd.
Category: otc | Type: HUMAN OTC DRUG LABEL
Date: 20241013

ACTIVE INGREDIENTS: CHONDRUS CRISPUS 3 g/100 g
INACTIVE INGREDIENTS: WATER 83.5 g/100 g

ACTIVE INGREDIENT

Chondrus Crispus Extract 3%

Snail Extract 3%

PURPOSE

whitening

INDICATIONS&USAGE

Firming and whitening skin
If used daily, it can enhance the moisturizing effect of the skin and make the skin look white

KEEP OUT OF REACH OF CHILDREN

If swallowed,get medical help or contact a Poison Control Center right away.

DO NOT USE

on damaged or broken skin

Stop use and ask a doctor if

rash occurs

When using this product

keep out of eyes.rinse with water to remove.

WARNINGS

For extermal use only.

DOSAGE & ADMINSTRATION

BID, 5-10g per dose
Ext.

Inactive ingredient

WATER